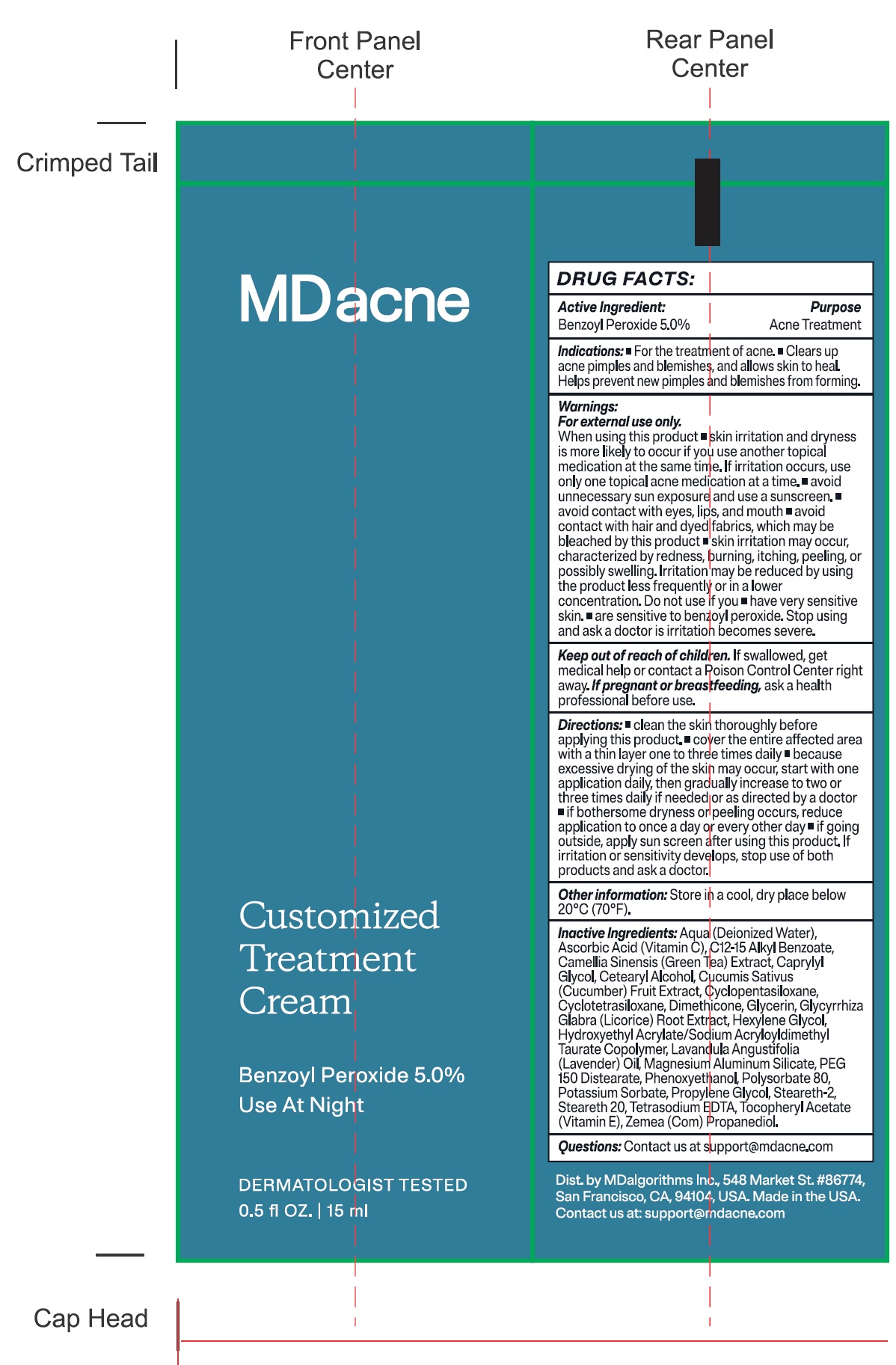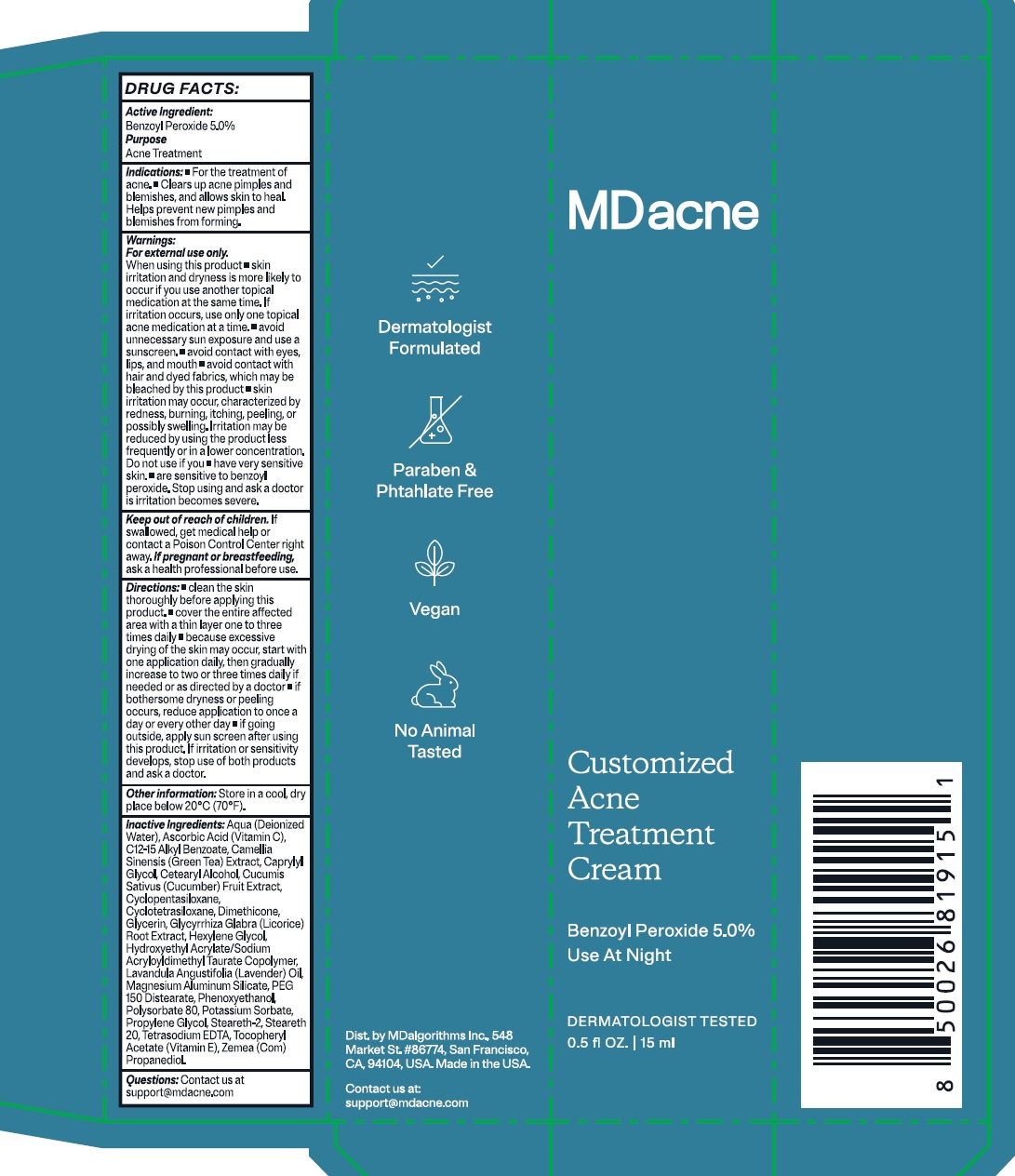 DRUG LABEL: MDacne Customized Acne Treatment Benzoyl Peroxide
NDC: 71804-536 | Form: CREAM
Manufacturer: MDAlgorithms Inc
Category: otc | Type: HUMAN OTC DRUG LABEL
Date: 20240926

ACTIVE INGREDIENTS: BENZOYL PEROXIDE 50 mg/1 mL
INACTIVE INGREDIENTS: WATER; ASCORBIC ACID; ALKYL (C12-15) BENZOATE; GREEN TEA LEAF; CAPRYLYL GLYCOL; CETOSTEARYL ALCOHOL; CUCUMBER; CYCLOMETHICONE 5; CYCLOMETHICONE 4; DIMETHICONE; GLYCERIN; GLYCYRRHIZA GLABRA; HEXYLENE GLYCOL; LAVENDER OIL; MAGNESIUM ALUMINUM SILICATE; PEG-150 DISTEARATE; PHENOXYETHANOL; POLYSORBATE 80; POTASSIUM SORBATE; PROPYLENE GLYCOL; STEARETH-2; STEARETH-20; EDETATE SODIUM; .ALPHA.-TOCOPHEROL ACETATE

MDacne Customized Acne Treatment Cream Benzoyl Peroxide 5.0%

Active Ingredient:

Benzoyl Peroxide 5.0%

Purpose

Acne Treatment

Indications:

- For the treatment of acne.
- Clears up acne pimples and blemishes, and allows skin to heal. Helps prevent new pimples and blemishes from forming.

Warnings:

For external use only.

When using this product

- skin irritation and dryness is more likely to occur if you use another topical medication at the same time. If irritation occurs, use only one topical acne medication at a time.
- avoid unnecessary sun expodure and use a sunscreen.
- avoid contact with eyes, lips, and mouth
- avoid contact with hair and dyed fabrics, which may be bleached by this product
- skin irritation may occur, characterized by redness, burning, itching, peeling, or possibly swelling. Irritation may be reduced by using the product less frequently or in a lower concentration.

Do not use if you

- have very sensitive skin.
- are sensitive to benzoyl peroxide.

Stop using and ask a doctor

is irritation becomes severe.

Keep out of reach of children.

If swallowed, get nedical help or contact a Poison Control Center right away.

If pregnant or breastfeeding,

ask a health professional before use.

Directions:

- clean the skin thoroughly before applying this product.
- cover the entire affected area with a thin layer one to three times daily
- because excessive drying of the skin may occur, start with one application daily, then gradually increase to two or three times daily if needed or as directed by a doctor
- if bothersome dryness or peeling occurs, reduce application to once a day or every other day
- if going outside, apply sun sunscreen after using this product. If irritation or sensitivity develops, stop use of both products and ask a doctor.

Other information:

Store in a cool, dry place below 20ºC (70ºF).

Inactive Ingredients:

Aqua (Deionized Water), Ascorbic Acid (Vitamin C), C12-15 Alkyl Benzoate, Camellia Sinensis (Green Tea) Extract, Caprylyl Glycol, Cetearyl Alcohol, Cucumis Sativus (Cucumber) Fruit Extract, Cyclopentasiloxane, Cyclotetrasiloxane, Dimethicone, Glycerin, Glycyrrhiza Glabra (Licorice) Root Extract, Hexylene Glycol, Hydroxyethyl Acrylate/Sodium Acryloyldimethyl Taurate Copolymer, Lavandula Angustifolia (Lavender) Oil, Magnesium Aluminum Silicate, PEG 150 Distearate, Phenoxyethanol, Polysorbate 80, Potassium Sorbate, Propylene Glycol, Steareth-2, Steareth 20, Tetrasodium EDTA, Tocopheryl Acetate (Vitamin E), Zemea (Com) Propanediol.

Questions:

Contact us at support@mdacne.com